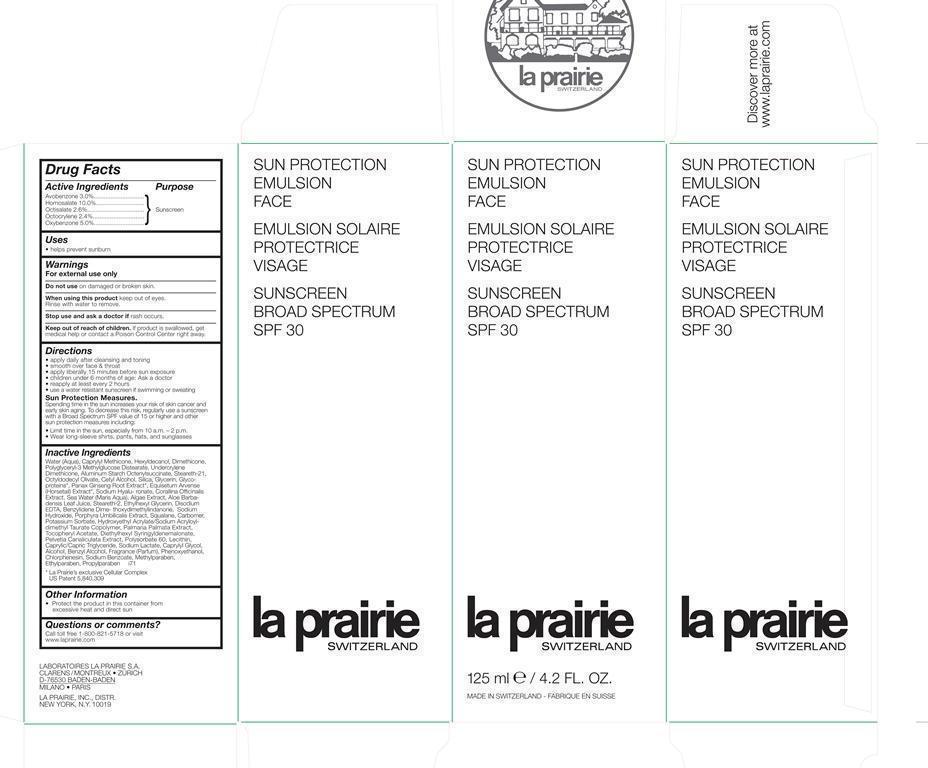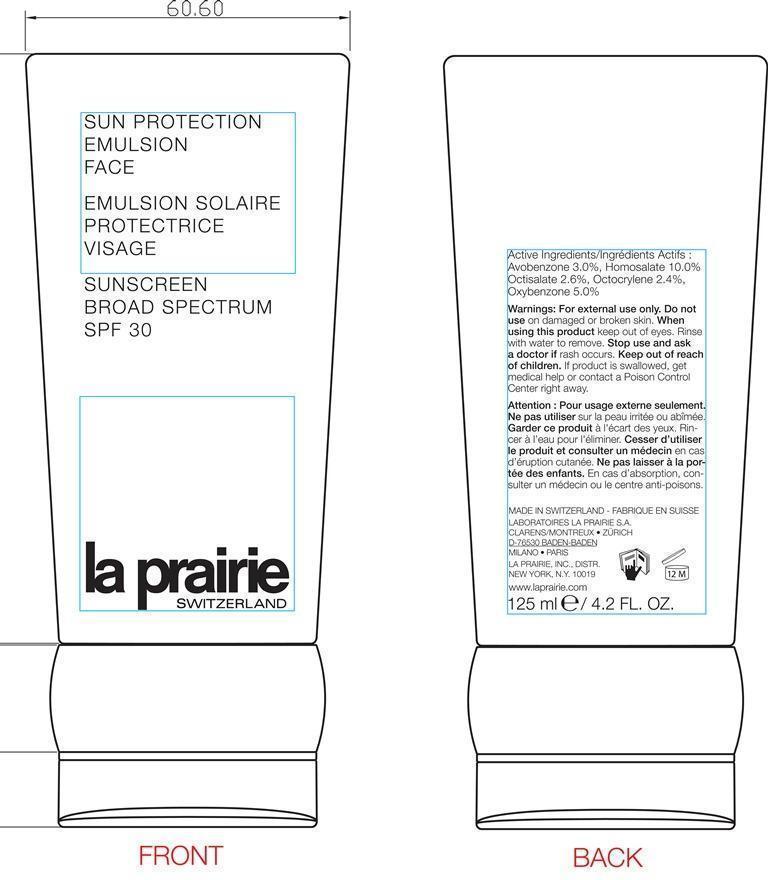 DRUG LABEL: Sun Protection Emulsion Face Broad Spectrum SPF 30
NDC: 68807-321 | Form: CREAM
Manufacturer: Temmentec Ag
Category: otc | Type: HUMAN OTC DRUG LABEL
Date: 20160125

ACTIVE INGREDIENTS: HOMOSALATE 10 g/100 kg; OCTISALATE 2.6 g/100 kg; OCTOCRYLENE 2.4 g/100 kg; OXYBENZONE 5 g/100 kg; AVOBENZONE 3 g/100 kg
INACTIVE INGREDIENTS: WATER; CAPRYLYL TRISILOXANE; HEXYLDECANOL; DIMETHICONE; STEARETH-21; CETYL ALCOHOL; SILICON DIOXIDE; GLYCERIN; ASIAN GINSENG; HYALURONATE SODIUM; CORALLINA OFFICINALIS; SODIUM CHLORIDE; ALOE VERA LEAF; STEARETH-2; ETHYLHEXYLGLYCERIN; EDETATE DISODIUM; BENZYLIDENE DIMETHOXYDIMETHYLINDANONE; SODIUM HYDROXIDE; SQUALANE; CARBOMER 934; POTASSIUM SORBATE; HYDROXYETHYL ACRYLATE/SODIUM ACRYLOYLDIMETHYL TAURATE COPOLYMER (45000 MPA.S AT 1%); DULSE; .ALPHA.-TOCOPHEROL ACETATE; DIETHYLHEXYL SYRINGYLIDENEMALONATE; PELVETIA CANALICULATA; POLYSORBATE 60; LECITHIN, SOYBEAN; MEDIUM-CHAIN TRIGLYCERIDES; SODIUM LACTATE; CAPRYLYL GLYCOL; ALCOHOL; BENZYL ALCOHOL; PHENOXYETHANOL; CHLORPHENESIN; SODIUM BENZOATE; METHYLPARABEN; ETHYLPARABEN; PROPYLPARABEN

Sun Protection Emulsion Face Broad Spectrum SPF 30

Active ingredients Purpose

Avobenzone 3.0% Sunscreen

Homosalate 10.0% Sunscreen

Octisalate 2.6% Sunscreen

Octocrylene 2.4% Sunscreen

Oxybenzone 5.0% Sunscreen

Uses

helps prevent sunburn

Keep out of reach of children. If product is swallowed, get medical help or contact a Poison Control Center right away.

Stop use and ask a doctor if rash occurs.

Warnings

For external use only

Do not use on damaged or broken skin

When using this product keep out of eyes . Rinse with water to remove.

Directions

- apply daily after cleansing and toning

- smooth over face & throat

- apply liberally 15 minutes before sun exposure

- children under 6 months of age: Ask a doctor

- reapply at least every 2 hours

- use a water resistant sunscreen if swimming or sweating

Sun Protection Measures.

Spending time in the sun increases your risk of skin cancer and

early skin aging. To decrease this risk, regularly use a sunscreen

with a Broad Spectrum SPF value of 15 or higher and other

sun protection measures including:

- Limit time in the sun, especially from 10 a.m. – 2 p.m.

- Wear long-sleeve shirts, pants, hats, and sunglasses

Inactive Ingredients

Water (Aqua), Caprylyl Methicone, Hexyldecanol, Dimethicone, Polyglyceryl-3 Methylglucose Distearate, Undercrylene Dimethicone, Aluminum Starch Octenylsuccinate, Steareth-21, Octyldodecyl Olivate, Cetyl Alcohol, Silica, Glycerin, Glycoproteins, Panax Ginseng Root Extract, Equisetum Arvense (Horsetail) Extract, Sodium Hyalu-ronate, Corallina Officinalis Extract, Sea Water (Maris Aqua), Algae Extract, Aloe Barbadensis Leaf Juice, Steareth-2, Ethylhexyl Glycerin, Disodium EDTA, Benzylidene Dime- thoxydimethylindanone, Sodium Hydroxide, Porphyra Umbilicalis Extract, Squalane, Carbomer, Potassium Sorbate, Hydroxyethyl Acrylate/Sodium Acryloyldimethyl Taurate Copolymer, Palmaria Palmata Extract, Tocopheryl Acetate, Diethylhexyl Syringyldenemalonate, Pelvetia Canaliculata Extract, Polysorbate 60, Lecithin, Caprylic/Capric Triglyceride, Sodium Lactate, Caprylyl Glycol, Alcohol, Benzyl Alcohol, Fragrance (Parfum), Phenoxyethanol, Chlorphenesin, Sodium Benzoate, Methylparaben, Ethylparaben, Propylparaben.

PACKAGE LABEL

Sun Protection Emulsion Face

Emulsion Solaire Protectrice Visage

Sunscreen Broad Spectrum SPF 30

La Prairie Switzerland

125 ml 4.2 Fl. Oz.